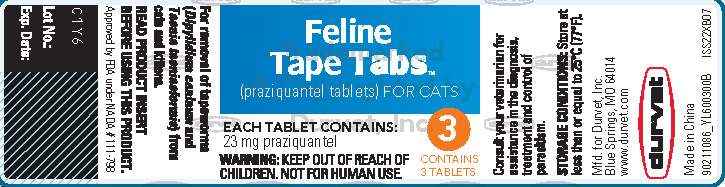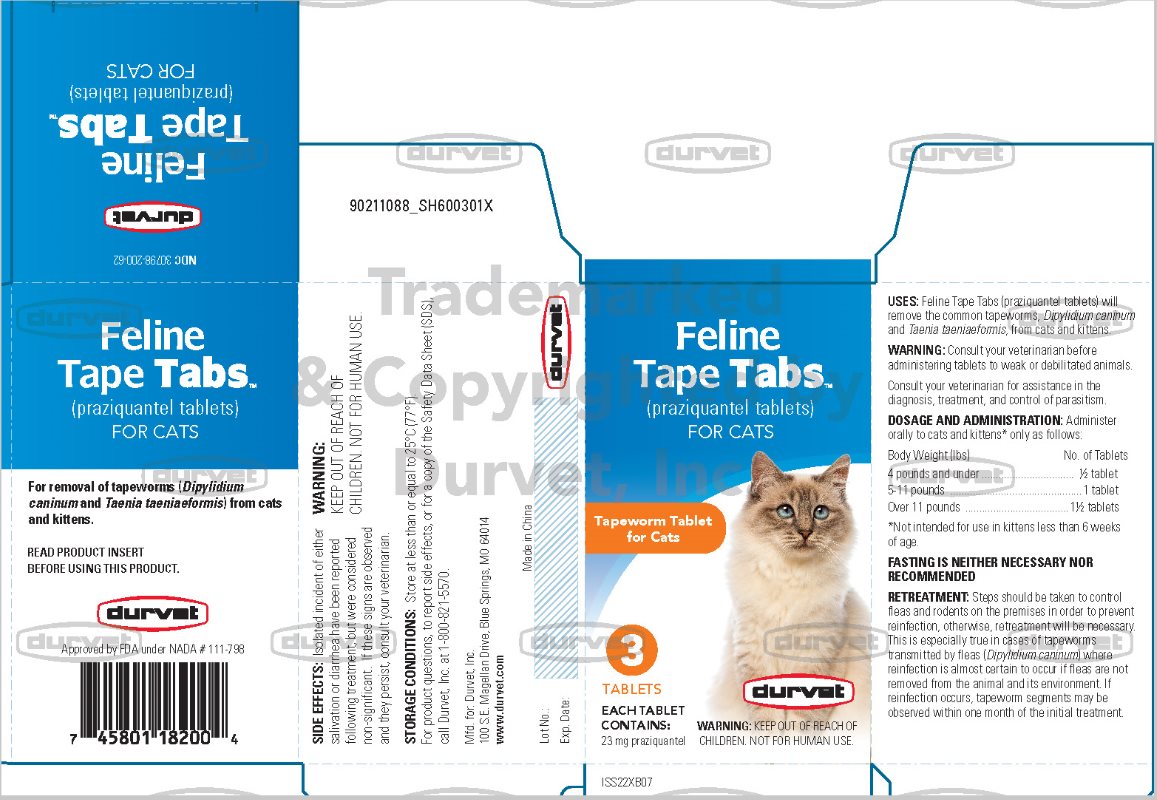 DRUG LABEL: Durvet Feline Tape Tabs
NDC: 30798-200 | Form: TABLET, CHEWABLE
Manufacturer: Durvet, Inc.
Category: animal | Type: OTC ANIMAL DRUG LABEL
Date: 20221221

ACTIVE INGREDIENTS: PRAZIQUANTEL 23 mg/1 1

durvet

Feline

Tape Tabs™

(praziquantel tablets) FOR CATS

Consult your veterinarian for assistance in the diagnosis, treatment and control of parasitism.

Consult your veterinarian before administering the tablets to weak or debilitated animals.

Each tablet contains 23 mg praziquantel.

DESCRIPTION:

Feline Tape Tabs (praziquantel tablets) are sized for easy oral administration to either adult cats or kittens. The tablets may be crumbled and mixed with the feed.

USES:

Feline Tape Tabs (praziquantel tablets) will remove the common tapeworms, Dipylidium caninum and Taenia taeniaeformis, from cats and kittens.

DOSAGE AND ADMINISTRATION:

Feline Tape Tabs (praziquantel tablets) may be given directly in the mouth or crumbled and mixed with the food. Administer to cats and kittens* only as follows:

Body Weight (lbs) | No. of Tablets
4 pounds and under | ½ tablet
5-11 pounds | 1 tablet
Over 11 pounds | 1 ½ tablets
*Not intended for use in kittens less than 6 weeks of age.

FASTING IS NEITHER NECESSARY NOR RECOMMENDED.

RETREATMENT:

Steps should be taken to control fleas and rodents on the premises in order to prevent reinfection; otherwise, retreatment will be necessary. This is especially true in cases of tapeworms transmitted by fleas (Dipylidium caninum) where reinfection is almost certain to occur if fleas are not removed from the animal and its environment. If reinfection occurs, tapeworm segments may be observed within one month of the initial treatment.

SIDE EFFECTS:

Isolated incident of either salivation or diarrhea have been reported following treatment, but were considered non-significant. If these signs are observed and they persist, consult your veterinarian.

Questions? For product questions, to report side effects, or for a copy of the Safety Data Sheet (SDS), call Durvet, Inc. at 1-800-821-5570.

For additional information about reporting side effects for animal drugs, contact FDA at 1-888-FDA-VETS or http://www.fda.gov/reportanimalae.

WARNING:

Keep out of the reach of children.
Not for human use.

HOW SUPPLIED:

Bottle of 3 scored tablets. Each scored tablet contains 23 mg praziquantel.

STORAGE CONDITIONS:

Store at less than or equal to 25°C (77°F).

durvet

Mfd. for: Durvet, Inc.
100 S.E. Magellan Drive
Blue Springs, MO 64014
www.durvet.com

ISS22XB07

Approved by FDA under NADA # 111-798

Made in China

90211089_PA600301X

Principal Display Panel

Feline

Tape Tabs™

(praziquantel tablets) FOR CATS

CONTAINS
3 TABLETS

EACH TABLET CONTAINS:
23 mg praziquantel

WARNING: KEEP OUT OF REACH OF
CHILDREN. NOT FOR HUMAN USE.

Feline

Tape Tabs™

(praziquantel tablets)

FOR CATS

Tapeworm Tablet
for Cats

3
TABLETS

EACH TABLET
CONTAINS:
23 mg praziquantel

durvet

WARNING: KEEP OUT OF REACH OF
CHILDREN. NOT FOR HUMAN USE.